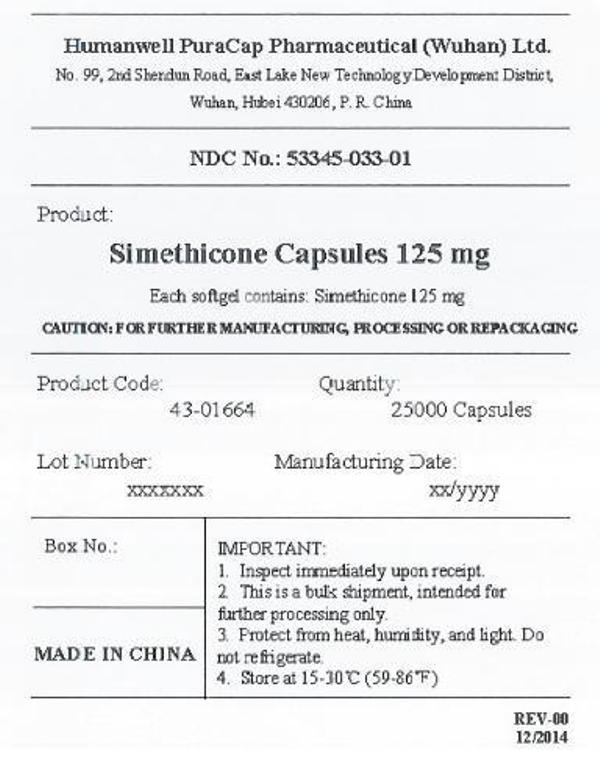 DRUG LABEL: Simethicone
NDC: 53345-033 | Form: CAPSULE, LIQUID FILLED
Manufacturer: Humanwell PuraCap Pharmaceutical (Wuhan) Co., Ltd.
Category: otc | Type: HUMAN OTC DRUG LABEL
Date: 20241125

ACTIVE INGREDIENTS: DIMETHICONE 125 mg/1 1
INACTIVE INGREDIENTS: FD&C BLUE NO. 1; FD&C RED NO. 40; D&C YELLOW NO. 10; GELATIN; GLYCERIN; PEPPERMINT OIL; WATER

SIMETHICONE CAPSULES 125 mg, liquid filled

Active ingredient (in each capsule)

Simethicone 125 mg

Purpose

Antigas

Uses

for relief of

- pressure, bloating, and fullness commonly referred to as gas

Warnings

Keep out of reach of children.

Directions

- adults: swallow with water 1 or 2 softgels as needed after meals and at bedtime
- do not exceed 4 softgels in 24 hours except under the advice and supervision of a physician

Other information

- store at room temperature 15°-30°C (59°-86°F)
- protect from light, heat and moisture

Inactive ingredients

D&C Yellow #10, FD&C Blue #1, FD&C Red #40, gelatin, glycerin, peppermint oil, purified water, and white edible ink

Manufactured by:
Humanwell PuraCap Pharmaceutical (Wuhan) Co., Ltd.
Wuhan, Hubei
430206, China

PRINCIPAL DISPLAY PANEL - Shipping Label

SIMETHICONE CAPSULES, 125 mg

Quantity : 25000 Capsules
NDC. No : 53345-033-01

IMPORTANT:
1.Inspect immediate upon receipt.
2.This is a bulk shipment, intended for further processing only.
3.Protect from heat, humidity, and light. Do not refrigerate.
4.Store at 15-30°C (59-86°F)

CAUTION : FOR FURTHER MANUFACTURING, PROCESSING OR REPACKAGING